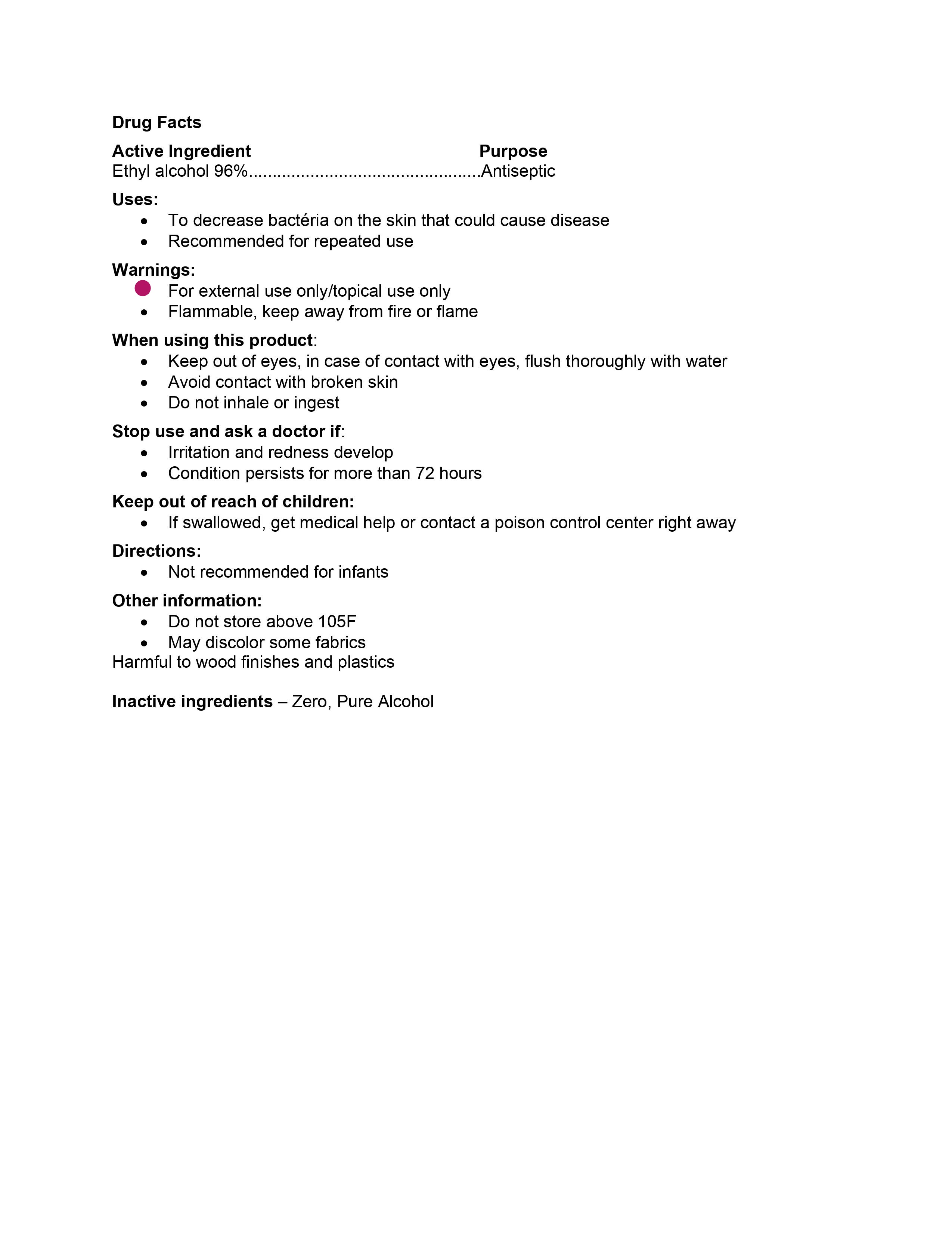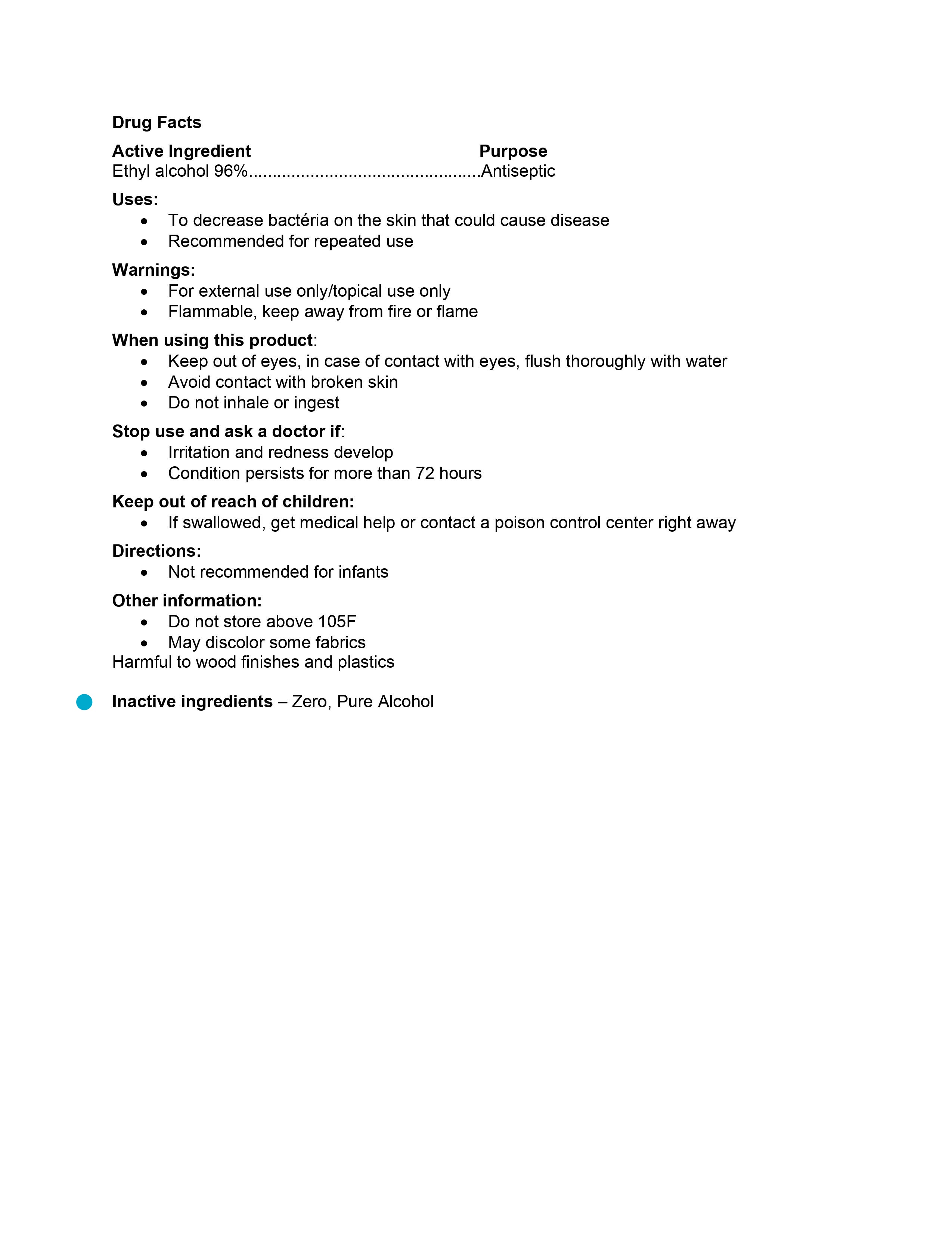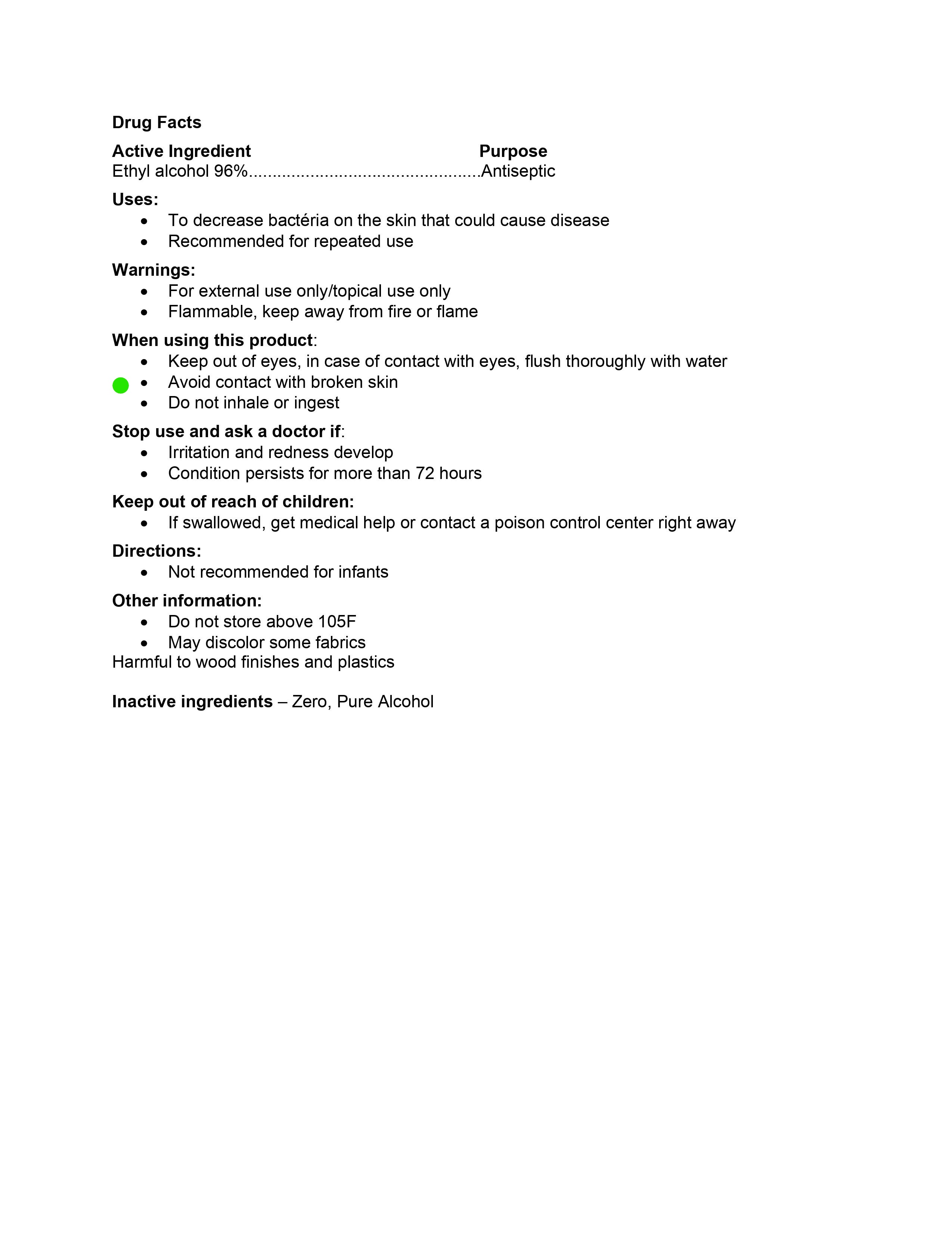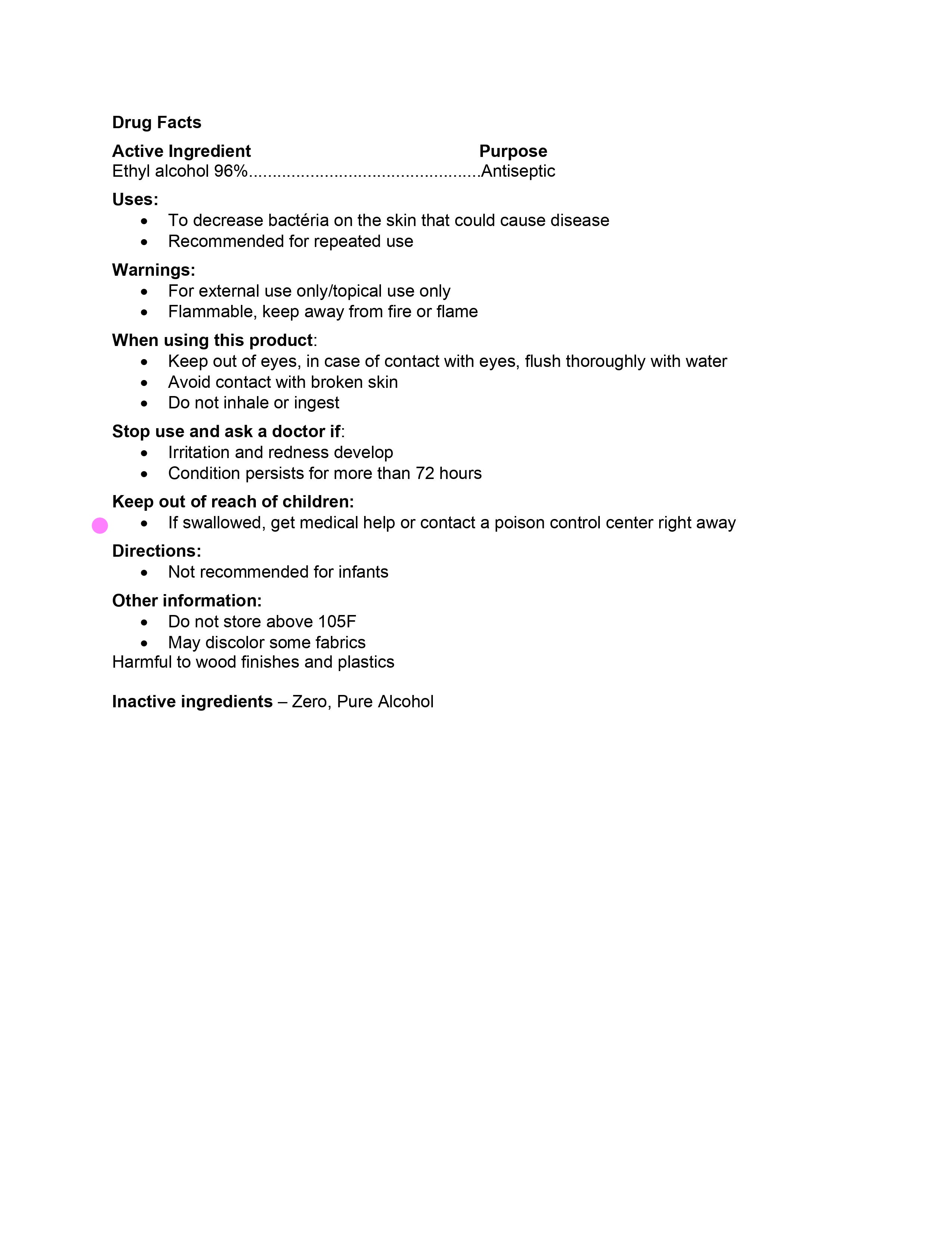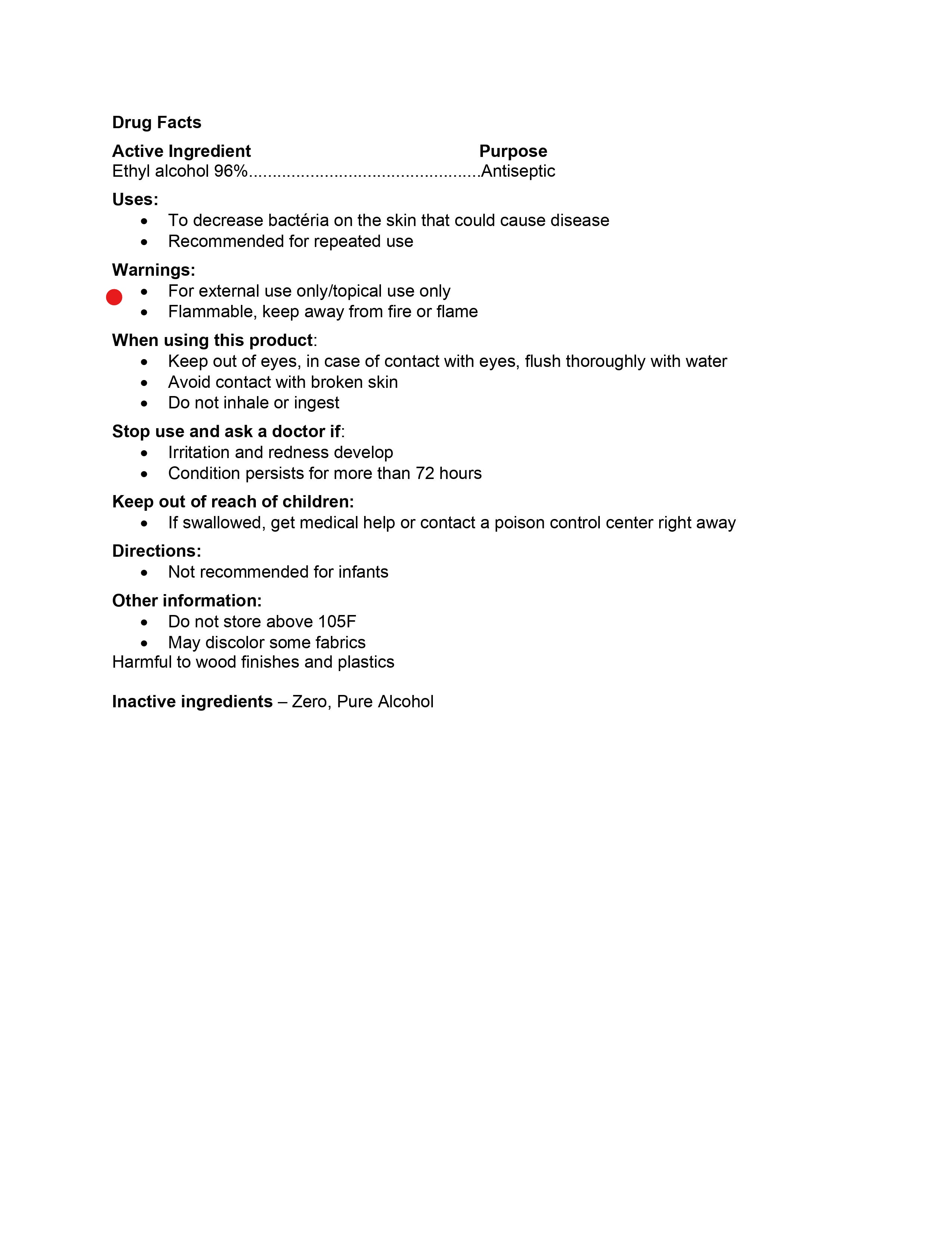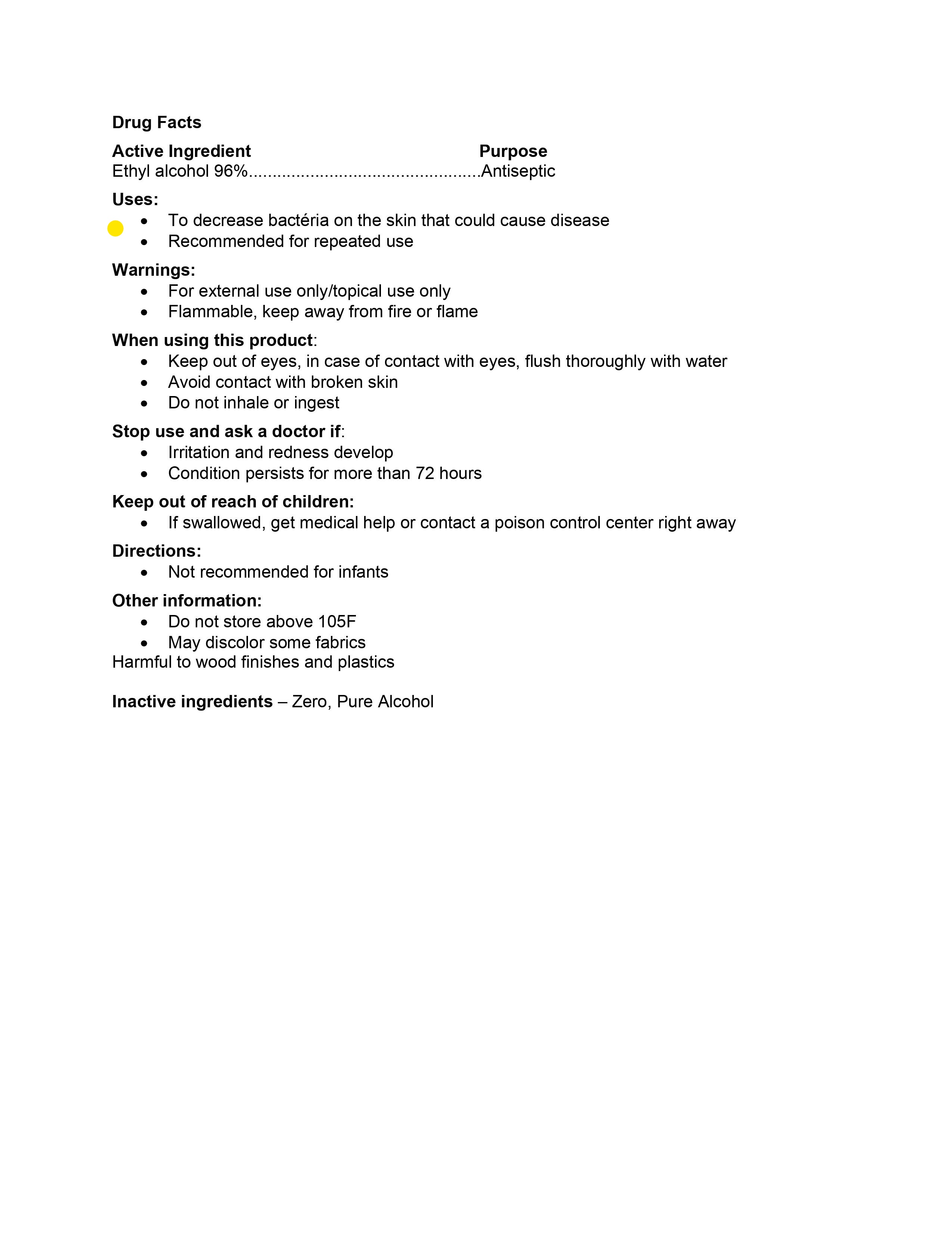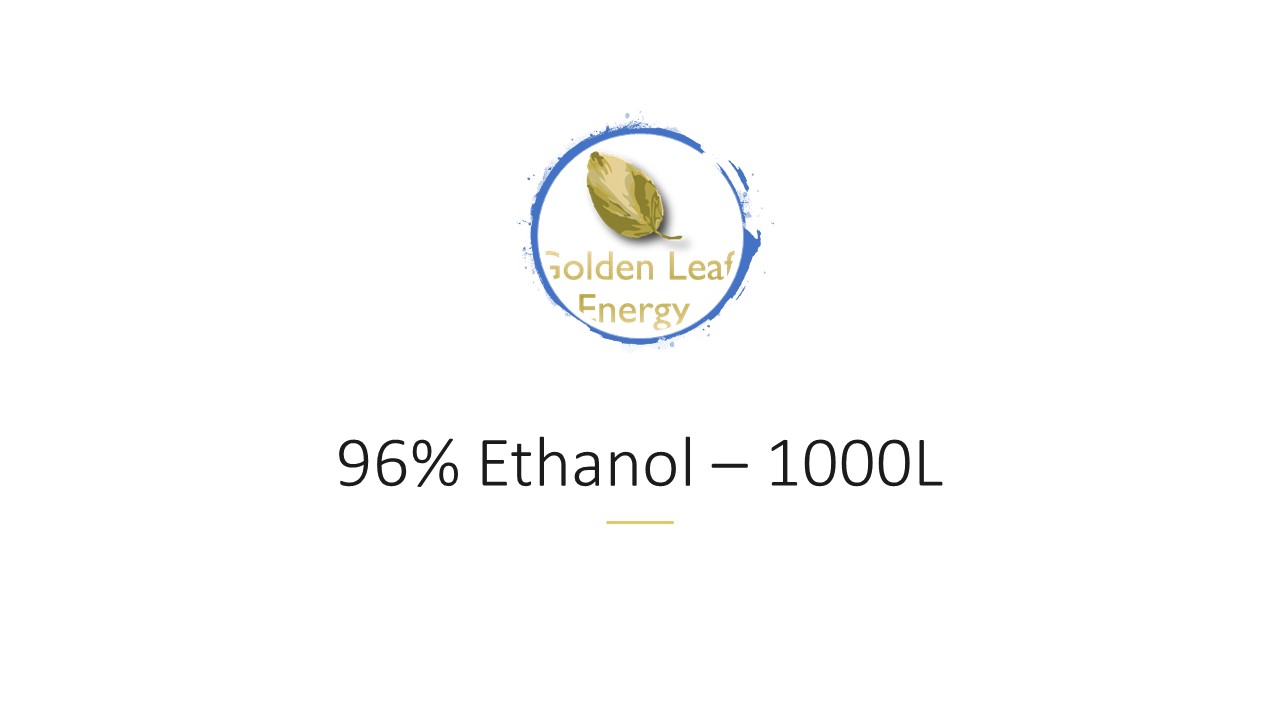 DRUG LABEL: Ethanol
NDC: 79137-001 | Form: LIQUID
Manufacturer: Golden Leaf Energy
Category: otc | Type: HUMAN OTC DRUG LABEL
Date: 20200619

ACTIVE INGREDIENTS: ALCOHOL 1 L/1 L
INACTIVE INGREDIENTS: WATER 1 L/1 L

Active ingredient - Ethanol

Ethanol

Drug Facts/Warnings

Drug Facts - Indications and usage

Drug Facts - Purpose

Drug Facts - Keep out of reach of children

Drug Facts - Inactive Ingredients

Drug Facts - Dosage

96% Ethanol - 1000L

1000 - Ethanol